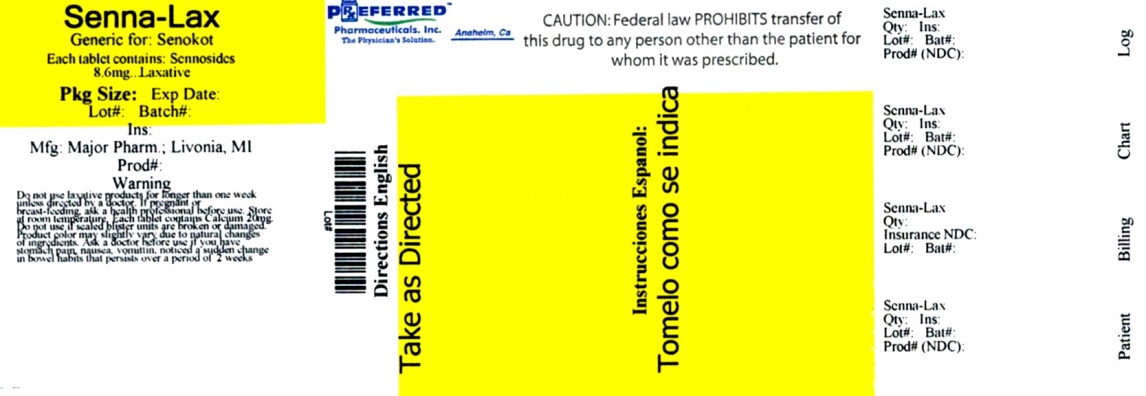 DRUG LABEL: Senna-Lax
NDC: 68788-6442 | Form: TABLET
Manufacturer: Preferred Pharmaceuticals Inc.
Category: otc | Type: HUMAN OTC DRUG LABEL
Date: 20170623

ACTIVE INGREDIENTS: SENNOSIDES A AND B 8.6 mg/1 1
INACTIVE INGREDIENTS: CROSCARMELLOSE SODIUM; DIBASIC CALCIUM PHOSPHATE DIHYDRATE; HYPROMELLOSE, UNSPECIFIED; MAGNESIUM SILICATE; MAGNESIUM STEARATE; MICROCRYSTALLINE CELLULOSE; LIGHT MINERAL OIL; POLYETHYLENE GLYCOL 400

Senna-Lax

Drug Facts

Active ingredient

(in each tablet)

Sennosides 8.6 mg

Purpose

Laxative

Uses

- relieves occasional constipation (irregularity)
- generally causes bowel movement in 6-12 hours

Warnings

Do not use

- laxative products for longer than one week unless directed by a doctor

Ask a doctor before use if you have

- stomach pain, nausea, or vomiting, noticed a sudden change in bowel habits that continues over a period of 2 weeks

Stop use and ask a doctor if

- you have rectal bleeding or fail to have a bowel movement after use of a laxative
These may indicate a serious condition.

If pregnant or breast-feeding,

ask a health care professional before use.

Keep out of reach of children.

In case of overdose, get medical help or contact a Poison Control Center right away.

Directions

- preferable at bedtime or a directed by a doctor
- adults and children 12 years of age and older: 2 tablets once a day: maximum of 4 tablets once a day
- children (6-12 years) 1tablet once a day: maximum 2 tablets once a day
- children (2-6 years) ½ tablet once a day: maximum 1 tablet once a day
- children under 2 years of age: Ask a doctor

Other information

- Store at room temperature, USP
- Each tablet contains: Calcium 20 mg

Inactive ingredient

Croscarmellose Sodium, Dicalcium Phosphate, Hypromellose, Magnesium Silicate, Magnesium Stearate, Microcrystalline Cellulose, Mineral Oil and Polyethylene Gycol

Questions or comments? (800) 616-2471

Tamper Evident:

Do not use if sealed blister units are broken or damaged.

Product color may slightly vary due to natural changes of ingredients

Manufactured by:
Contract Pharmacal Corp.
135 Adams Avenue
Hauppauge, NY 11788 USA
www.cpc.com

Distributed By:

MAJOR® PHARMACEUTICALS

31778 Enterprise Drive

Livonia, MI 48150

Rev. 10/15

Repackaged By: Preferred Pharmaceuticals Inc.

Principal Display Panel

Senna-Lax

(Standardized Senna Concentrate)

8.6 mg Sennosides

100 Tablets